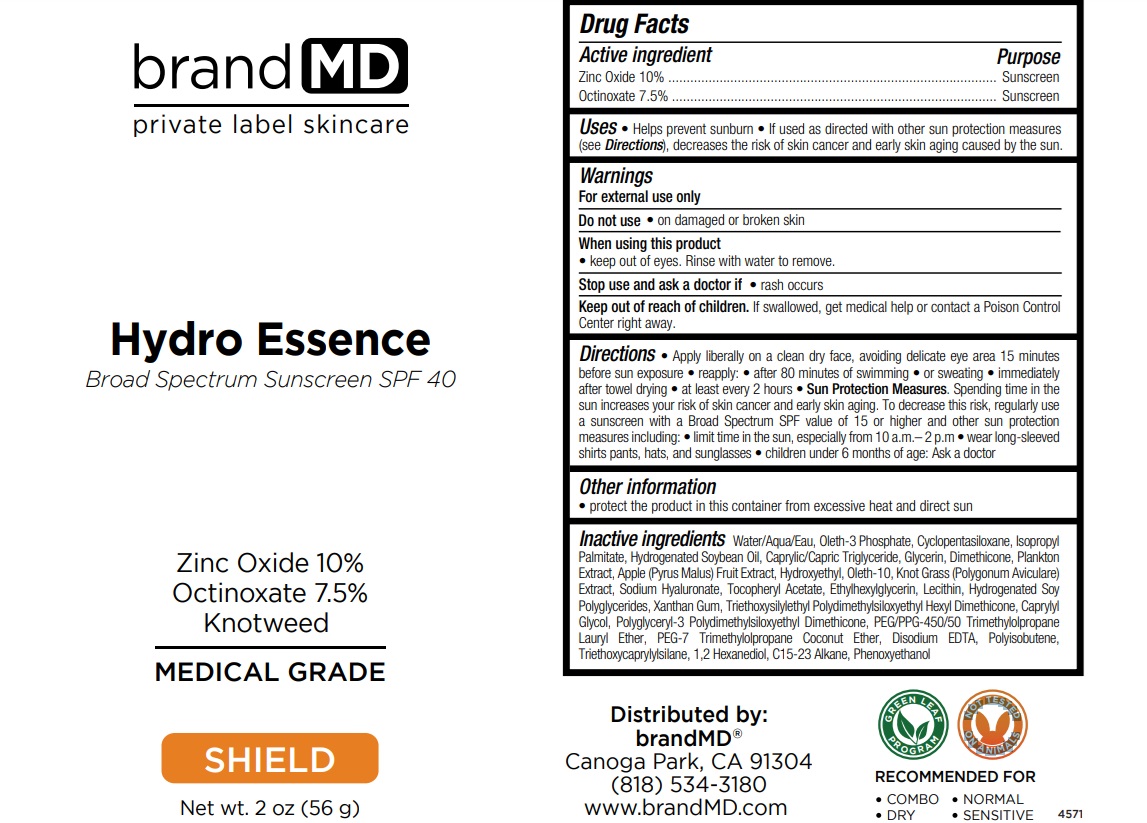 DRUG LABEL: Hydro Essence Broad Spectrum Sunscreen SPF 40
NDC: 72957-008 | Form: CREAM
Manufacturer: Private Label Skin Care
Category: otc | Type: HUMAN OTC DRUG LABEL
Date: 20250225

ACTIVE INGREDIENTS: ZINC OXIDE 10 g/100 g; OCTINOXATE 7.5 g/100 g
INACTIVE INGREDIENTS: WATER; OLETH-3 PHOSPHATE; CYCLOMETHICONE 5; ISOPROPYL PALMITATE; HYDROGENATED SOYBEAN OIL; MEDIUM-CHAIN TRIGLYCERIDES; GLYCERIN; DIMETHICONE, UNSPECIFIED; APPLE; HYDROXYETHYL ACRYLATE/SODIUM ACRYLOYLDIMETHYL TAURATE COPOLYMER (100000 MPA.S AT 1.5%); OLETH-10; POLYGONUM AVICULARE TOP; HYALURONATE SODIUM; .ALPHA.-TOCOPHEROL ACETATE; ETHYLHEXYLGLYCERIN; SOYBEAN LECITHIN; XANTHAN GUM; TRIETHOXYSILYLETHYL POLYDIMETHYLSILOXYETHYL HEXYL DIMETHICONE; CAPRYLYL GLYCOL; POLYGLYCERYL-3 POLYDIMETHYLSILOXYETHYL DIMETHICONE (4000 MPA.S); PEG-7 TRIMETHYLOLPROPANE COCONUT ETHER; EDETATE DISODIUM; POLYISOBUTYLENE (1000 MW); TRIETHOXYCAPRYLYLSILANE; 1,2-HEXANEDIOL; C15-23 ALKANE; PHENOXYETHANOL

Hydro Essence Broad Spectrum Sunscreen SPF 40

Active ingredient

Zinc Oxide 10%

Octinoxate 7.5%

Purpose

Sunscreen

Uses

• Helps prevent sunburn • If used as directed with other sun protection measures (see Directions), decreases the risk of skin cancer and early skin aging caused by the sun.

Warnings

For external use only

Do not use • on damaged or broken skin

When using this product
• keep out of eyes. Rinse with water to remove.

Stop use and ask a doctor if • rash occurs

Keep out of reach of children. If swallowed, get medical help or contact a Poison Control Center right away.

Directions

• Apply liberally on a clean dry face, avoiding delicate eye area 15 minutes before sun exposure • reapply: • after 80 minutes of swimming • or sweating. • immediately after towel dryings • at least every 2 hours • Sun Protection Measures. Spending time in the sun increases your risk of skin cancer and early skin aging. To decrease this risk, regularly use a sunscreen with a Broad Spectrum SPF value of 15 or higher and other sun protection measures including: • limit time in the sun, especially from 10 a.m.– 2 p.m • wear long-sleeved shirts pants, hats, and sunglasses • children under 6 months of age: Ask a doctor

Other information

• protect the product in this container from excessive heat and direct sun

Inactive ingredients

Water/Aqua/Eau, Oleth-3 Phosphate, Cyclopentasiloxane, Isopropyl Palmitate, Hydrogenated Soybean Oil, Caprylic/Capric Triglyceride, Glycerin, Dimethicone, Plankton Extract, Apple (Pyrus Malus) Fruit Extract, Hydroxyethyl, Oleth-10, Knot Grass (Polygonum Aviculare) Extract, Sodium Hyaluronate, Tocopheryl Acetate, Ethylhexylglycerin, Lecithin, Hydrogenated Soy Polyglycerides, Xanthan Gum, Triethoxysilylethyl Polydimethylsiloxyethyl Hexyl Dimethicone, Caprylyl Glycol, Polyglyceryl-3 Polydimethylsiloxyethyl Dimethicone, PEG/PPG-450/50 Trimethylolpropane Lauryl Ether, PEG-7 Trimethylolpropane Coconut Ether, Disodium EDTA, Polyisobutene, Triethoxycaprylylsilane, 1,2 Hexanediol, C15-23 Alkane, Phenoxyethanol

brand MD

Zinc Oxide 10%
Octinoxate 7.5%
Knotweed

MEDICAL GRADE
SHIELD

RECOMMENDED FOR
• COMBO • NORMAL
• DRY • SENSITIVE

GREEN LEAF PROGRAM
NOT TESTED ON ANIMALS

Distributed by:
brandMD®
Canoga Park, CA 91304
(818) 534-3180
www.brandMD.com